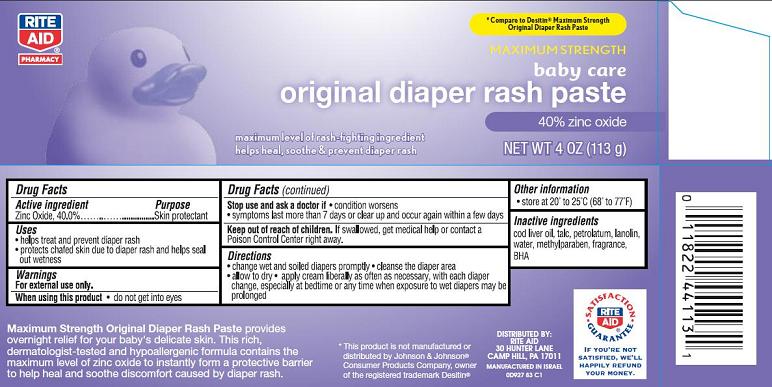 DRUG LABEL: Maximum Strength Original Diaper Rash
NDC: 11822-9271 | Form: CREAM
Manufacturer: Rite Aid Corporation
Category: otc | Type: HUMAN OTC DRUG LABEL
Date: 20140307

ACTIVE INGREDIENTS: ZINC OXIDE 40 g/100 g
INACTIVE INGREDIENTS: COD LIVER OIL; TALC; PETROLATUM; LANOLIN; WATER; METHYLPARABEN; BUTYLATED HYDROXYANISOLE

Maximum Strength Original Diaper Rash Paste

Active ingredient

Zinc Oxide........40.0%

Purpose

Skin protectant

Uses

- helps treat and prevent diaper rash
- protects chafed skin due to diaper rash and helps seal out wetness

Warnings

For external use only.

When using this product

- do not get into eyes

Stop use and ask a doctor if

- condition worsens
- symptoms last more than 7 days or clear up and occur again within a few days

Keep Out of Reach of Children.

If swallowed, get medical help or contact a Poison Control Center right away.

Directions

- change wet and soiled diapers promptly
- cleanse the diaper area
- allow to dry
- apply cream liberally as often as necessary, with each diaper change, especially at bedtime or any time when exposure to wet diapers may be prolonged

Other Information

- store at 20° to 25°C (68° to 77°F)

Inactive ingredients

cod liver oil, talc, petrolatum, lanolin, water, methylparaben, fragrance, BHA

Package/Label Principal Display Panel

Maximum Strength original diaper rash paste
40% zinc oxide

maximum level of rash-lighting ingredient
helps heal, soothe & prevent diaper rash

NET WT 4 OZ. (113 g)

*Compare to Desitin® Maximum Strength Original Diaper Rash Paste

Maximum Strength Original Diaper Rash Paste provides overnight relief for your baby’s delicate skin. This rich, dermatologist-tested and hypoallergenic formula contains the maximum level of zinc oxide to instantly form a protective barrier to help heal and sooth discomfort caused by diaper rash.

*This product is not manufactured or distributed by Johnson & Johnson®
Consumer Products Company, owner of the registered trademark Desitin®

DISTRIBUTED BY:
RITE AID,
30 HUNTER LANE
CAMP HILL, PA 17011

MADE IN ISRAEL

0D927 B3 C1

SATISFACTION GUARANTEE

IF YOU’RE NOT SATISFIED, WE’LL HAPPILY REFUND YOUR MONEY.

Carton Label